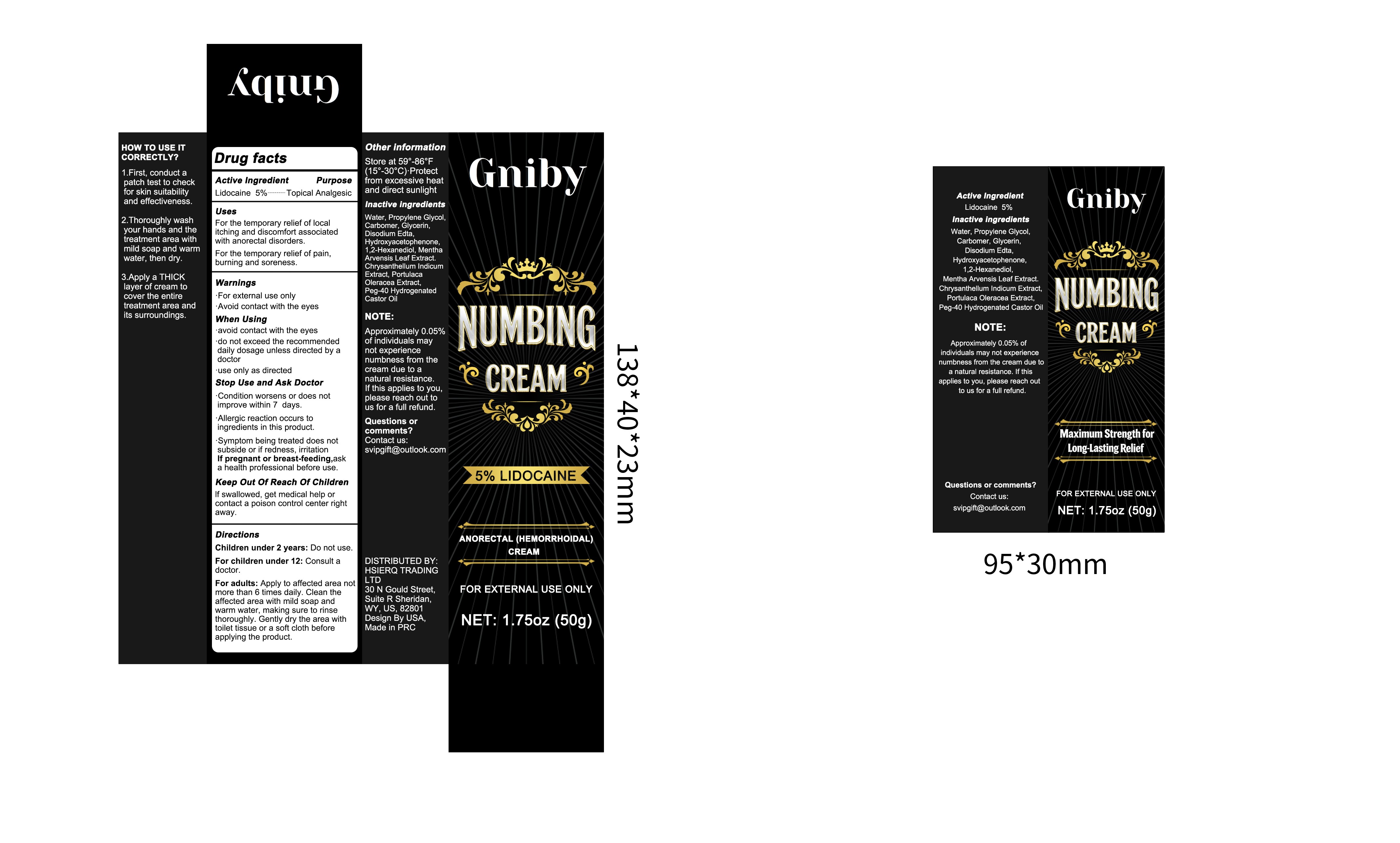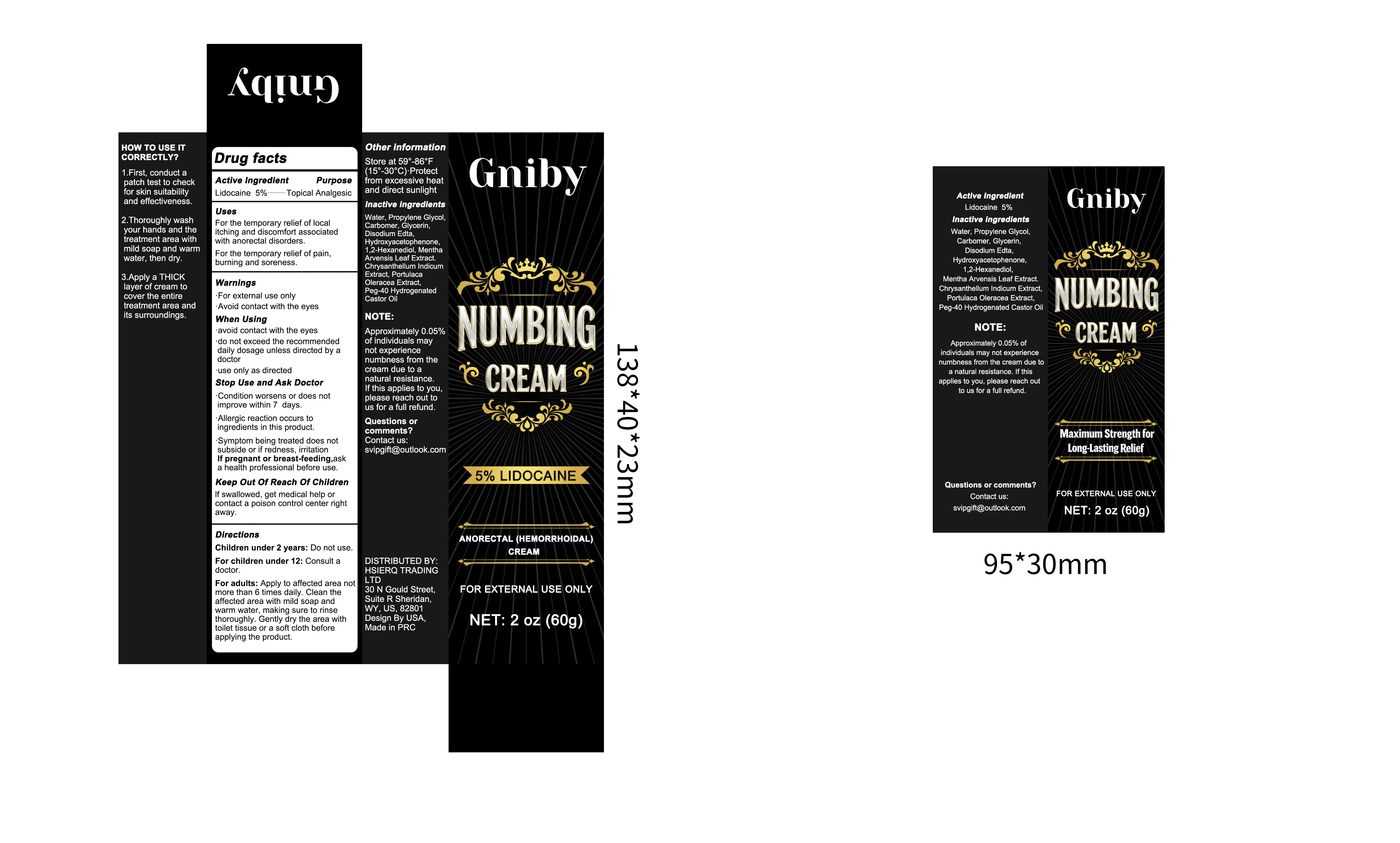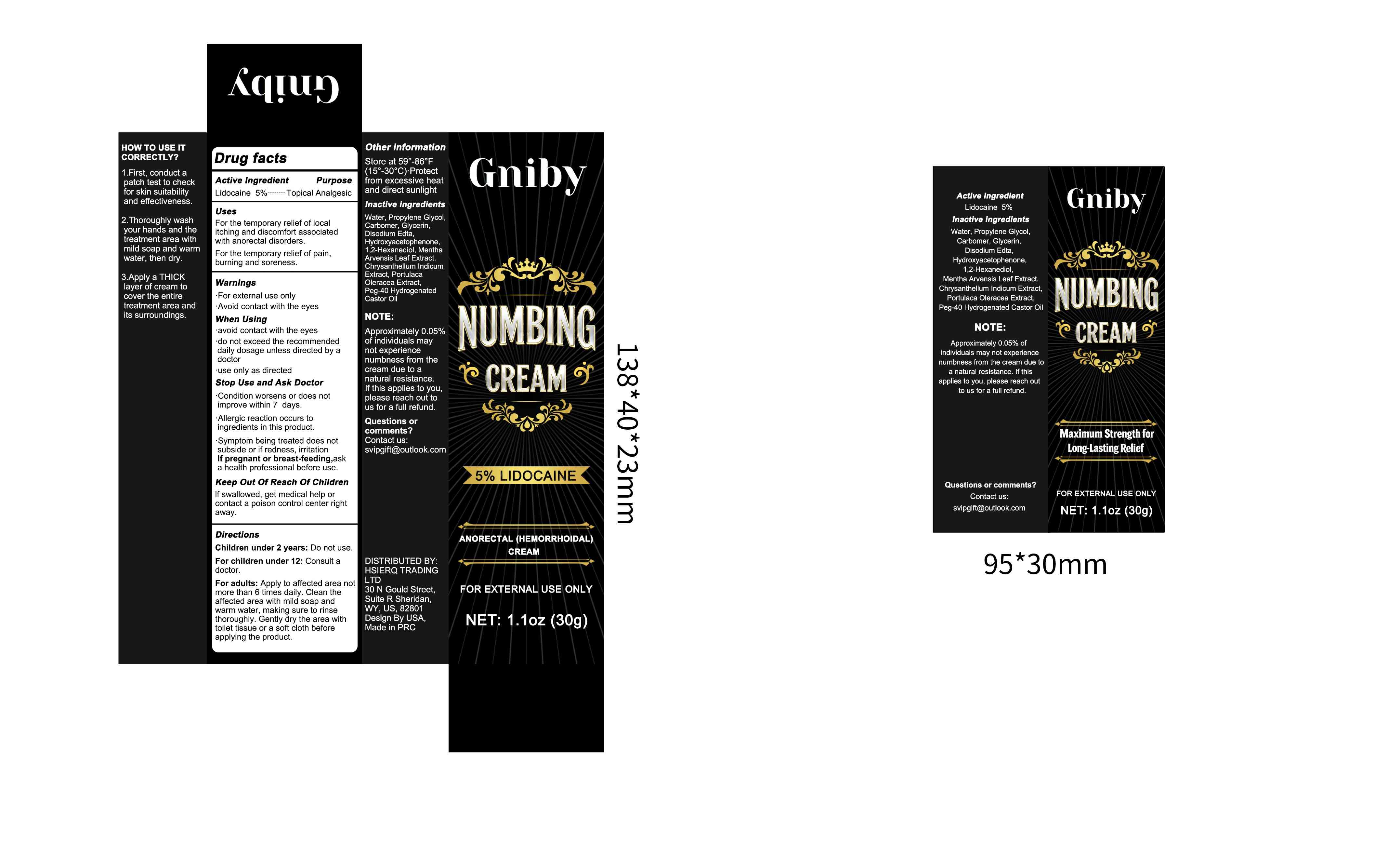 DRUG LABEL: Gniby - LIDOCAINE  ANORECTAL HEMORRHOIDAL
NDC: 87152-002 | Form: CREAM
Manufacturer: Putian Licheng District Zhijiancheng Trading Co., Ltd.
Category: otc | Type: HUMAN OTC DRUG LABEL
Date: 20260210

ACTIVE INGREDIENTS: LIDOCAINE 5 g/100 g
INACTIVE INGREDIENTS: 1,2-HEXANEDIOL; HYDROXYACETOPHENONE; PROPYLENE GLYCOL; EDETATE DISODIUM; WATER; PEG-40 HYDROGENATED CASTOR OIL; PURSLANE; MENTHA ARVENSIS LEAF; CHRYSANTHELLUM INDICUM TOP; GLYCERIN; CARBOMER

87152-002 Numbing Cream

ACTIVE INGREDIENT

Lidocaine 5%-----..-Topical Analgesic

Uses
For the temporary relief of localitching and discomfort associatedwith anorectal disorders.For the temporary relief of pain,burning and soreness.

KEEP OUT OF REACH OF CHILDREN

Keep Out Of Reach Of ChildrenIf swallowed, get medical help orcontact a poison control center rightaway.

Warnings.

For external use only·Avoid contact with the eyes

INACTIVE INGREDIENT

Water
PROPYLENE GLYCOL
CARBOMER
GLYCERIN
DISODIUM EDTA
HYDROXYACETOPHENONE
1,2-HEXANEDIOL
MENTHA ARVENSIS LEAF EXTRACT
CHRYSANTHELLUM INDICUM EXTRACT
PORTULACA OLERACEA EXTRACT
PEG-40 HYDROGENATED CASTOR OIL

INDICATIONS AND USAGE

Condition worsens or does notimprove within 7 days.Allergic reaction occurs toingredients in this product.Symptom being treated does notsubside or if redness, irritationIf pregnant or breast-feeding,aska health professional before use.

DOSAGE AND ADMINISTRATION

Children under 2 years: Do not use.For children under 12: Consult adoctor.
For adults: Apply to affected area notmore than 6 times daily. Clean theaffected area with mild soap andwarm water, making sure to rinsethoroughly. Gently dry the area withtoilet tissue or a soft cloth beforeapplying the product.